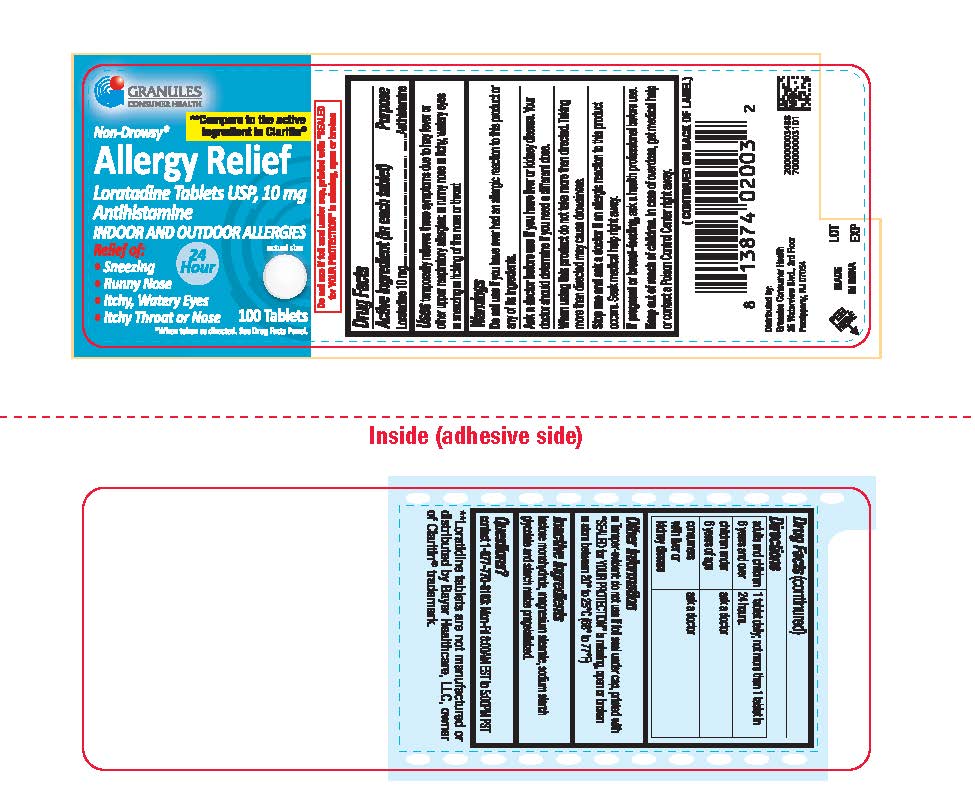 DRUG LABEL: Loratadine
NDC: 69848-019 | Form: TABLET
Manufacturer: GRANULES USA, INC.
Category: otc | Type: HUMAN OTC DRUG LABEL
Date: 20251222

ACTIVE INGREDIENTS: LORATADINE 10 mg/1 1
INACTIVE INGREDIENTS: MAGNESIUM STEARATE; LACTOSE MONOHYDRATE; STARCH, CORN; SODIUM STARCH GLYCOLATE TYPE A POTATO

Non-Drowsy
Allergy Relief
Loratadine Tablets, USP 10 mg
Antihistamine
Indoor and Outdoor Allergies
Relief of:
.Sneezing
.Runny Nose
.Itchy, Watery Eyes
.Itchy Throat or Nose

Active ingredient (in each tablet)

Loratadine 10 mg

Purpose

Antihistamine

Uses

temporarily relieves these symptoms due to hay fever or other upper respiratory allergies: ■ runny nose ■ itchy, watery eyes ■ sneezing ■ itching of the nose or throat

Do not use

if you have ever had an allergic reaction to this product or any of its ingredients.

Ask a doctor before use if you have

liver or kidney disease. Your doctor should determine if you need a different dose.

When using this product

do not take more than directed. Taking more than directed may cause drowsiness.

Stop use and ask a doctor if

an allergic reaction to this product occurs. Seek medical help right away.

If pregnant or breast-feeding,

ask a health professional before use.

Keep out of reach of children.

In case of overdose, get medical help or contact a Poison Control Center right away.

Directions

■adults and children6 years and over: 1 tablet daily; not more than 1 tablet in 24 hours.

■children under 6 years of age: ask a doctor
■consumers with liver or kidney disease: ask a doctor

Other information

■ Tamper-evident: do not use if foil seal under cap, printed with “SEALED for YOUR PROTECTION” is missing, open or broken
■ store between 20° to 25°C (68° to 77°F)

Inactive ingredients

lactose monohydrate, magnesium stearate, sodium starch glycolate and starch maize pregelatinized.

Questions?

contact 1-877-770-3183: Mon-Fri 8:00AM EST to 5:00PM PST